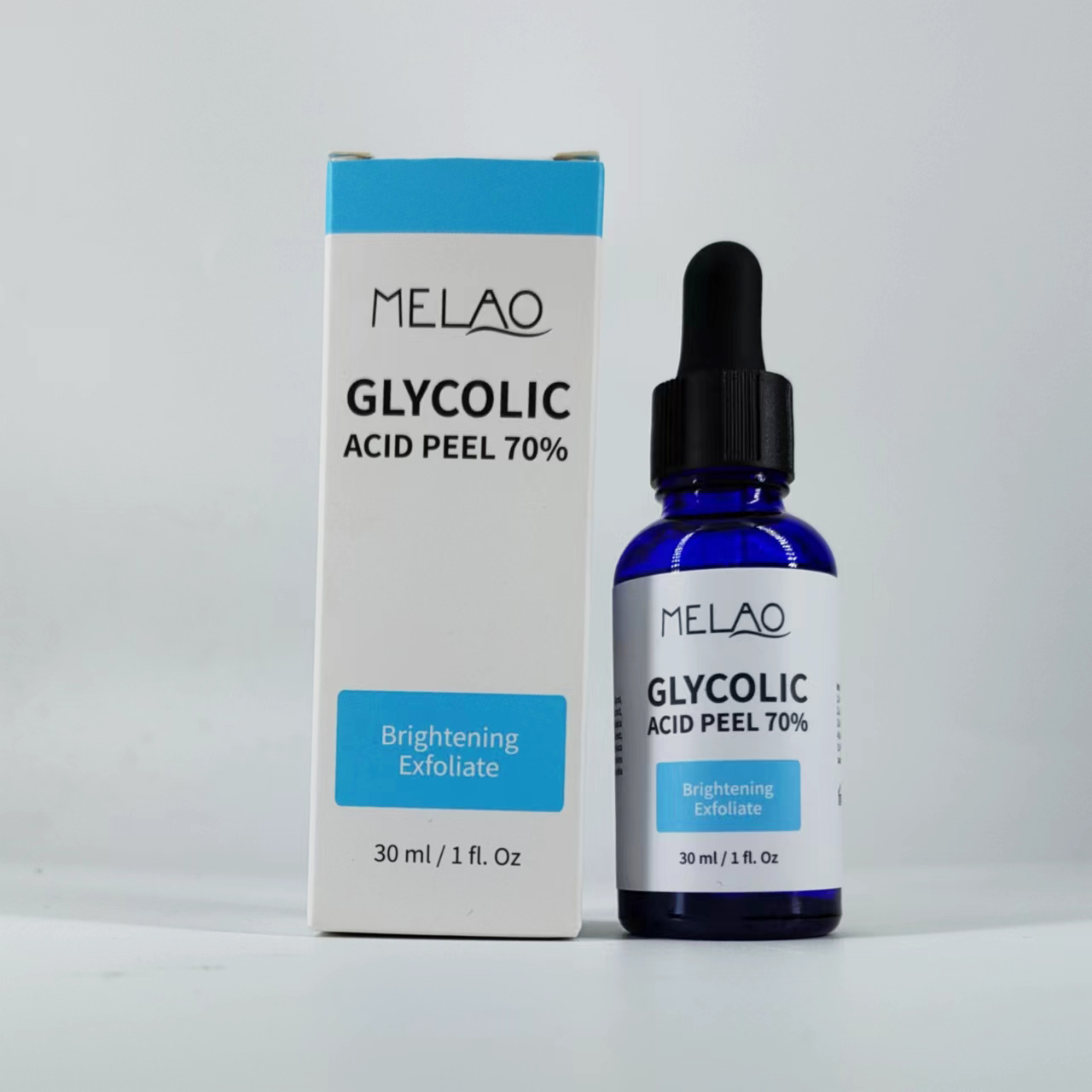 DRUG LABEL: MELAO GLYCOLIC ACID PEEL 70%
NDC: 74458-108 | Form: LIQUID
Manufacturer: Guangzhou Yilong Cosmetics Co., Ltd
Category: otc | Type: HUMAN OTC DRUG LABEL
Date: 20241222

ACTIVE INGREDIENTS: ROSMARINUS OFFICINALIS (ROSEMARY) LEAF OIL 0.3 g/100 mL; CENTELLA ASIATICA TRITERPENOIDS 0.15 g/100 mL
INACTIVE INGREDIENTS: ALOE VERA LEAF; SODIUM HYALURONATE; AQUA; PROPYLENE GLYCOL; SUGARCANE; CHRYSANTHELLUM INDICUM TOP; SOPHORA FLAVESCENS ROOT; PURSLANE

MELAO GLYCOLIC ACID PEEL 70%

ACTIVE INGREDIENT

Rosmarinus Officinalis (Rosemary) Leaf Extract

Centella Asiatica Extract

INACTIVE INGREDIENT

Aqua

Sodium Hyaluronate

Propylene Glycol

Saccharum Officinarum (Sugarcane) Extract

Chrysanthellum Indicum Extract

Sophora Angustifolia Root Extract

Portulaca Oleracea Extract

Pelargonium Graveolens Extract

Aloe Barbadensis Leaf Extract

Mentha Arvensis Extract

PURPOSE

Moisturizing

INDICATIONS AND USAGE

1.Wash your face with mild soap and
water. 2. Apply a thin layer. 3. Wait 1 to 5 minutes. 4. Wash your
face. 5.Pat dry and apply moisturizer and sunscreen.

WARNINGS

For external use only.

Stop use and ask a doctor if rash occurs.

Do not use on damaged or broken skin.

When using this product keep out of eyes. Rinse with water to remove.

Keep out of reach of children. If swallowed, get medical help or contact a Poison Control Center right away.

DOSAGE AND ADMINISTRATION

1.Wash your face with mild soap and
water. 2. Apply a thin layer. 3. Wait 1 to 5 minutes. 4. Wash your
face. 5.Pat dry and apply moisturizer and sunscreen.